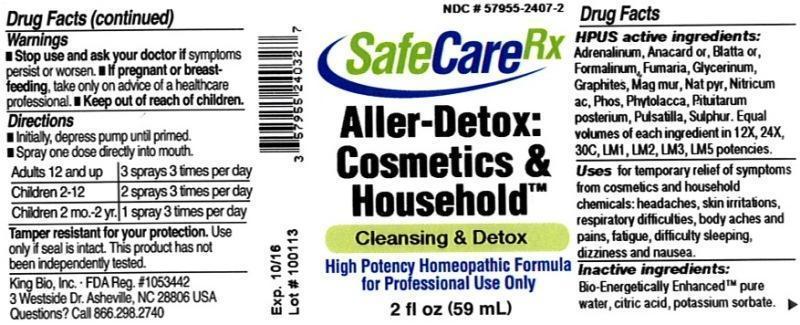 DRUG LABEL: Aller-Detox Cosmetics and Household
NDC: 57955-2407 | Form: LIQUID
Manufacturer: King Bio Inc.
Category: homeopathic | Type: HUMAN OTC DRUG LABEL
Date: 20131120

ACTIVE INGREDIENTS: EPINEPHRINE 12 [hp_X]/59 mL; SEMECARPUS ANACARDIUM JUICE 12 [hp_X]/59 mL; BLATTA ORIENTALIS 12 [hp_X]/59 mL; FORMALDEHYDE 12 [hp_X]/59 mL; FUMARIA OFFICINALIS FLOWERING TOP 12 [hp_X]/59 mL; GLYCERIN 12 [hp_X]/59 mL; GRAPHITE 12 [hp_X]/59 mL; MAGNESIUM CHLORIDE 12 [hp_X]/59 mL; SODIUM PYRUVATE 12 [hp_X]/59 mL; NITRIC ACID 12 [hp_X]/59 mL; PHOSPHORUS 12 [hp_X]/59 mL; PHYTOLACCA AMERICANA ROOT 12 [hp_X]/59 mL; SUS SCROFA PITUITARY GLAND 12 [hp_X]/59 mL; PULSATILLA VULGARIS 12 [hp_X]/59 mL; SULFUR 12 [hp_X]/59 mL
INACTIVE INGREDIENTS: WATER; CITRIC ACID MONOHYDRATE; POTASSIUM SORBATE

Aller-Detox: Cosmetics & Household

Drug Facts

____________________________________________________________________________________________________________________

HPUS active ingredients: Adrenalinum, Anacardium orientale, Blatta orientalis, Formalinum, Fumaria officinalis, Glycerinum, Graphites, Magnesia muriatica, Natrum pyruvicum, Nitricum acidum, Phosphorus, Phytolacca decandra, Pituitarum posterium, Pulsatilla, Sulphur. Equal volumes of each ingredient in 12X, 24X, 30C, LM1, LM2, LM3, LM5 potencies.

INDICATIONS AND USAGE

Uses for temporary relief of symptoms from cosmetics and household chemicals: headaches, skin irritations, respiratory difficulties, body aches and pains, fatigue, difficulty sleeping, dizziness and nausea.

INACTIVE INGREDIENT

Inactive ingredients: Bio-Energetically Enhanced pure water, citric acid, potassium sorbate.

Warnings

- Stop use and ask your doctor if symptoms persist or worsen.
- If pregnant or breast-feeding, take only on advice of a healthcare professional.

- Keep out of reach of children.

Directions:

- Initially, depress pump until primed.
- Spray one dose directly into mouth.
- Adults 12 and up 3 sprays 3 times per day.
- Children 2-12- 2 sprays 3 times per day.
- Children 2 mo.-2yr.- 1 spray 3 times per day.

OTHER SAFETY INFORMATION

Tamper resistant for your protection. Use only if safety seal is intact. This product has not been independently tested.

PURPOSE

Uses for temporary relief of symptoms from cosmetics and household chemicals:

- headaches
- skin irritations
- respiratory difficulties
- body aches and pains
- fatigue
- difficulty sleeping
- dizziness and nausea